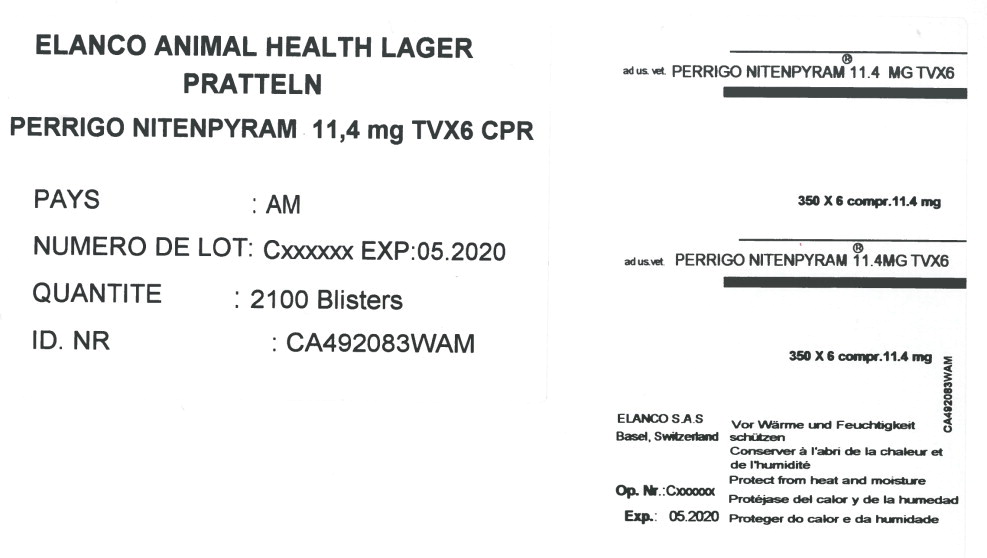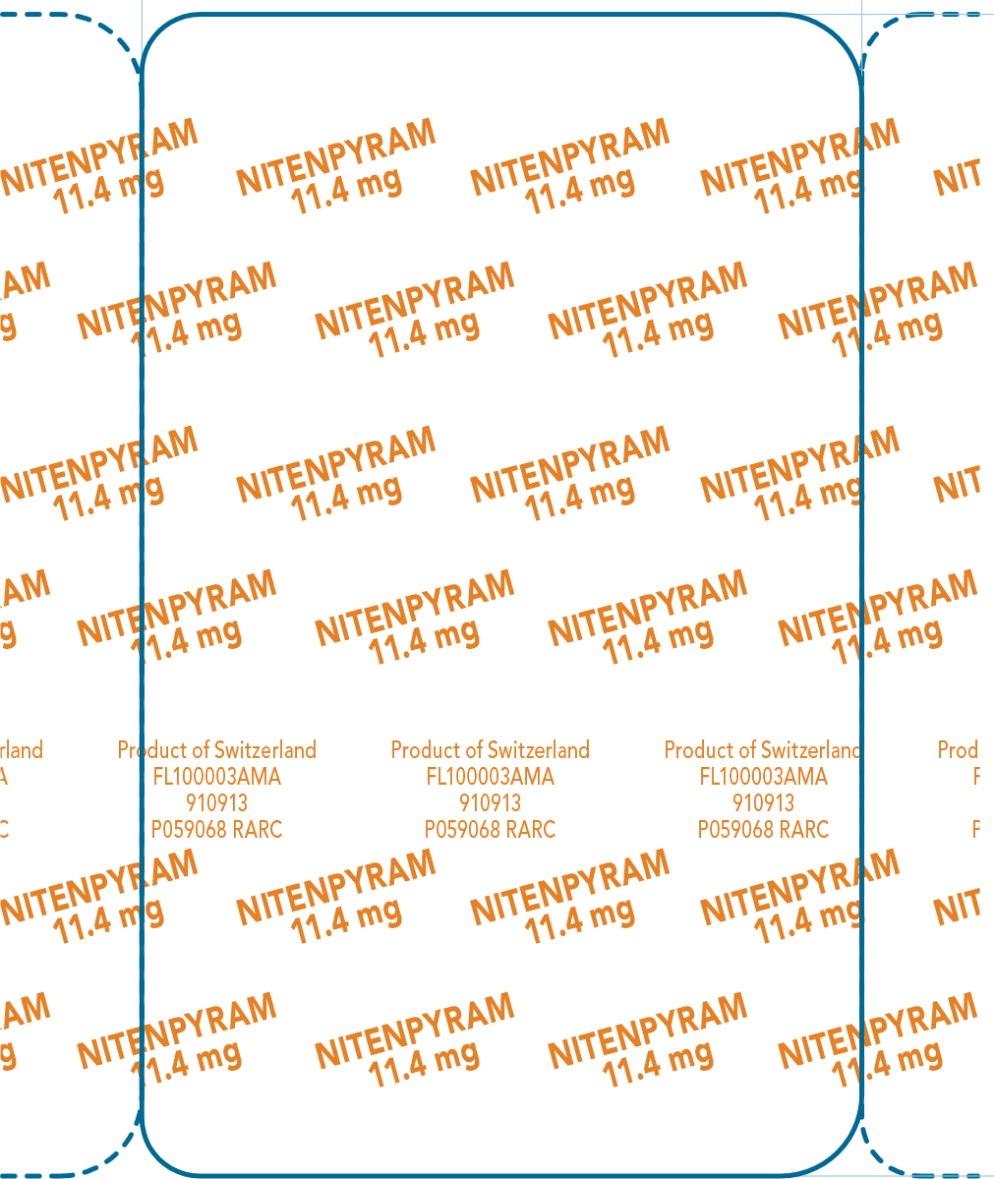 DRUG LABEL: Nitenpyram
NDC: 21091-880 | Form: CAPSULE
Manufacturer: Sergeant's Pet Care Products Inc.
Category: other | Type: BULK INGREDIENT - ANIMAL DRUG
Date: 20171120

ACTIVE INGREDIENTS: Nitenpyram 11.4 mg/1 1
INACTIVE INGREDIENTS: LACTOSE MONOHYDRATE; CELLULOSE, MICROCRYSTALLINE; STARCH, CORN; SILICON DIOXIDE; MAGNESIUM STEARATE

Principal Display Panel - Capguard 11.4 Shipping Label

ELANCO ANIMAL HEALTH LAGER
PRATTELN

PERRIGO NITENPYRAM 11,4 mg TVX 6 CPR

PAYS: AM

NUMERO DE LOT: Cxxxxxx EXP: 05.2020

QUANTITE: 2100 Blisters

ID. NR: CA4920832WAM

Principal Display Panel - Capguard 11.4 Blister Label

NITENPYRAM
11.4 mg

Product of Switzerland

FL100003AMA

910913

P059068 RARC